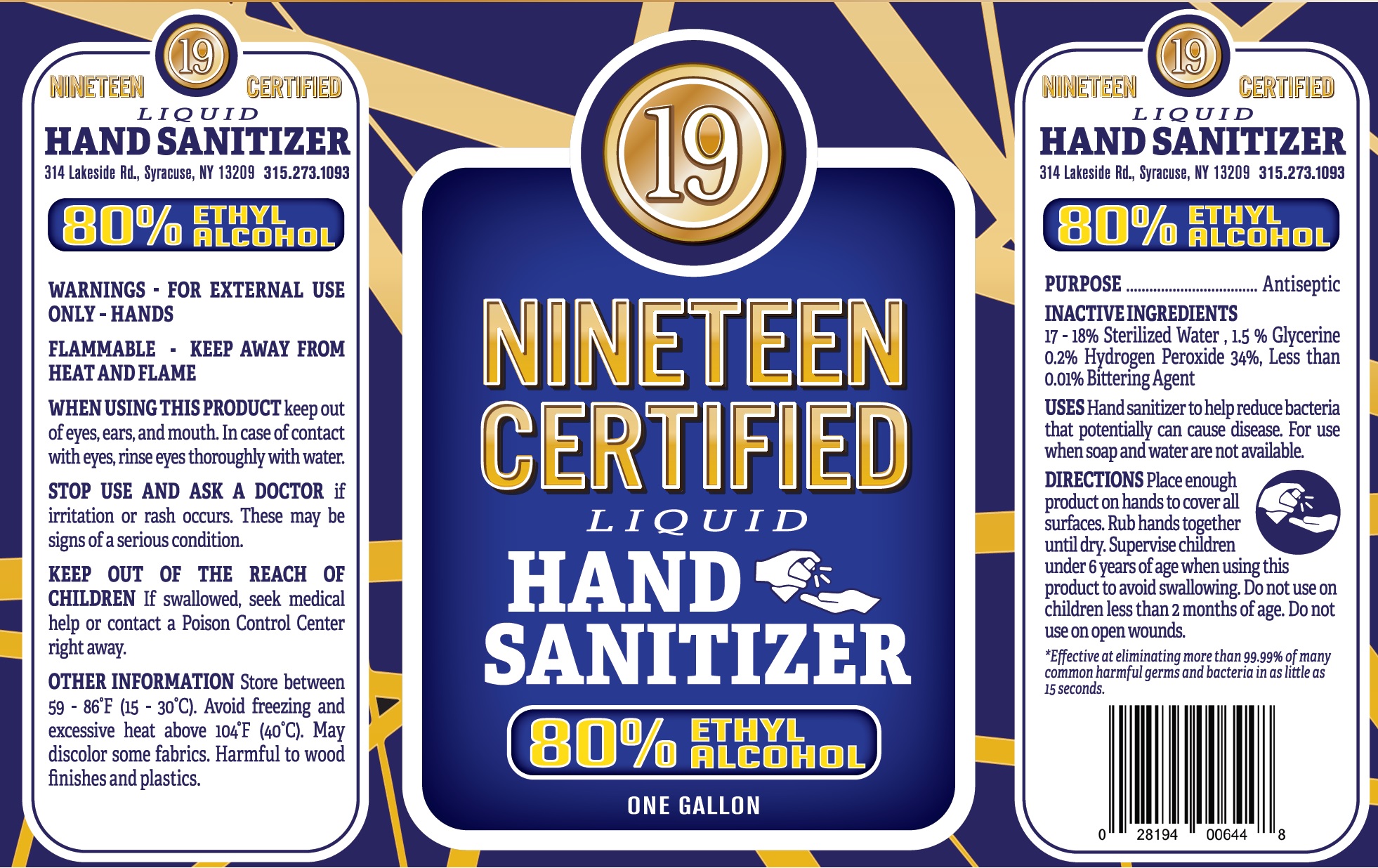 DRUG LABEL: Nineteen Certified Hand Sanitizer
NDC: 79526-000 | Form: LIQUID
Manufacturer: Lopez-Scripa Industries LLC
Category: otc | Type: HUMAN OTC DRUG LABEL
Date: 20200812

ACTIVE INGREDIENTS: ALCOHOL 0.8 mL/1 mL
INACTIVE INGREDIENTS: WATER; GLYCERIN; HYDROGEN PEROXIDE

Nineteen Certified Hand Sanitizer

ACTIVE INGREDIENT

ETHYL ALCOHOL 80%

PURPOSE

Antiseptic

INACTIVE INGREDIENTS

17-18% Sterilized Water, 1.5 % Glycerin 0.2% Hydrogen Peroxide 34%, Less than 0.01% Bittering Agent

USES

Hand anitizer to help reduce bacteria that potentially can cause disease. For use when soap and water are not available.

DIRECTIONS

Place enough product on hands to cover all surfaces. Rub hands together until dry. Supervise children under 6 years of age when using this product to avoid swallowing. Do not use on children less than 2 months of age. Do not use on open wounds.

WARNINGS

FOR EXTERNAL USE ONLY - HANDS

FLAMMABLE - KEEP AWAY FROM HEAT AND FLAME

WHEN USING THIS PRODUCT

keep out of eyes, ears, and mouth. In case of contact with eyes, rinse eyes thoroughly with water.

STOP USE AND ASK A DOCTOR

if irritation or rash occurs. These may be signs of a serious condition.

KEEP OUT OF THE REACH OF CHILDREN

If swallowed, seek medical help or contact a Poison Control Center right away.

OTHER INFORMATION

Store between 59-86°F (15-30°C). Avoid freezing and excessive heat above 104°F (40°C). May discolor some fabrics. Harmful to wood finishes and plastics.